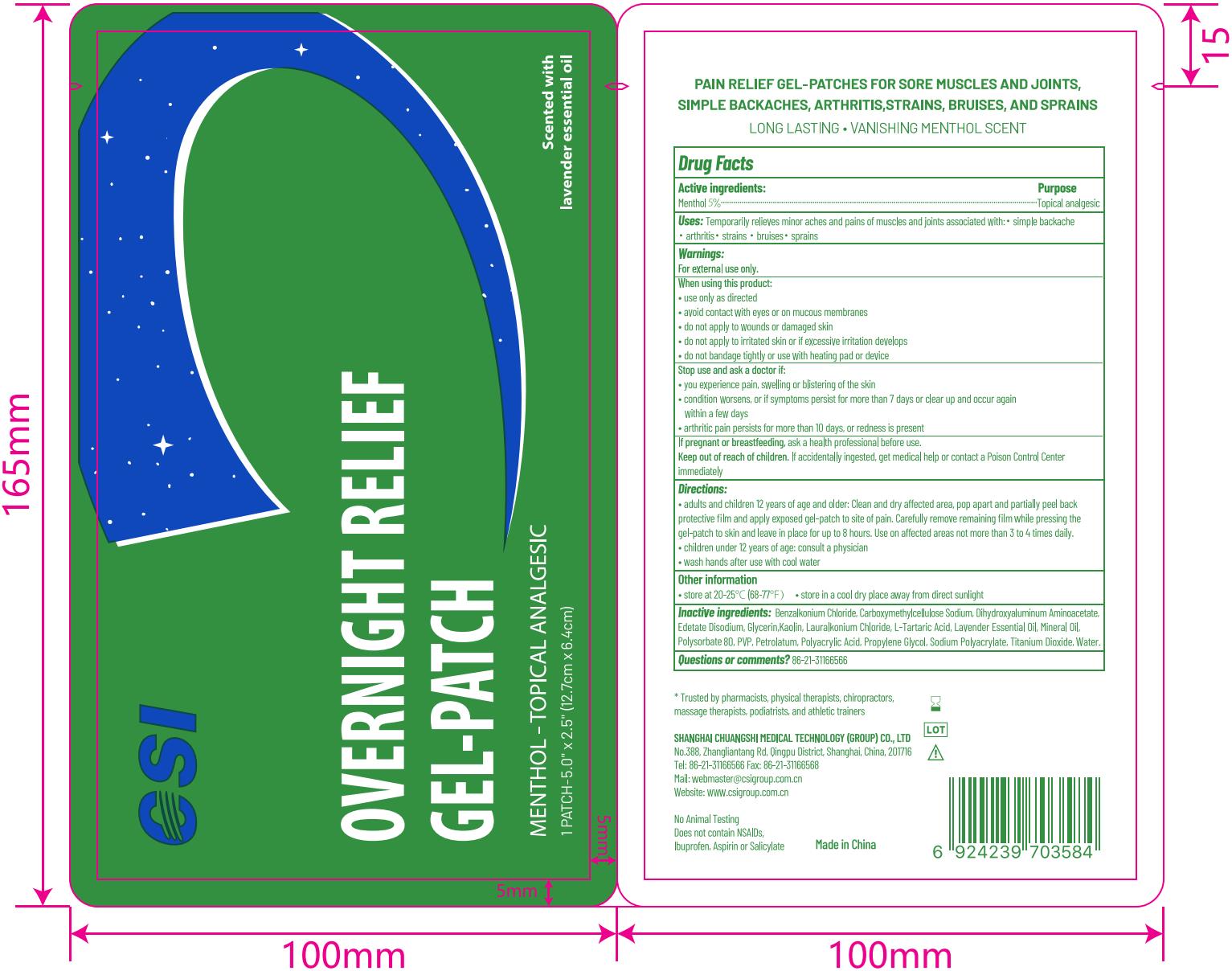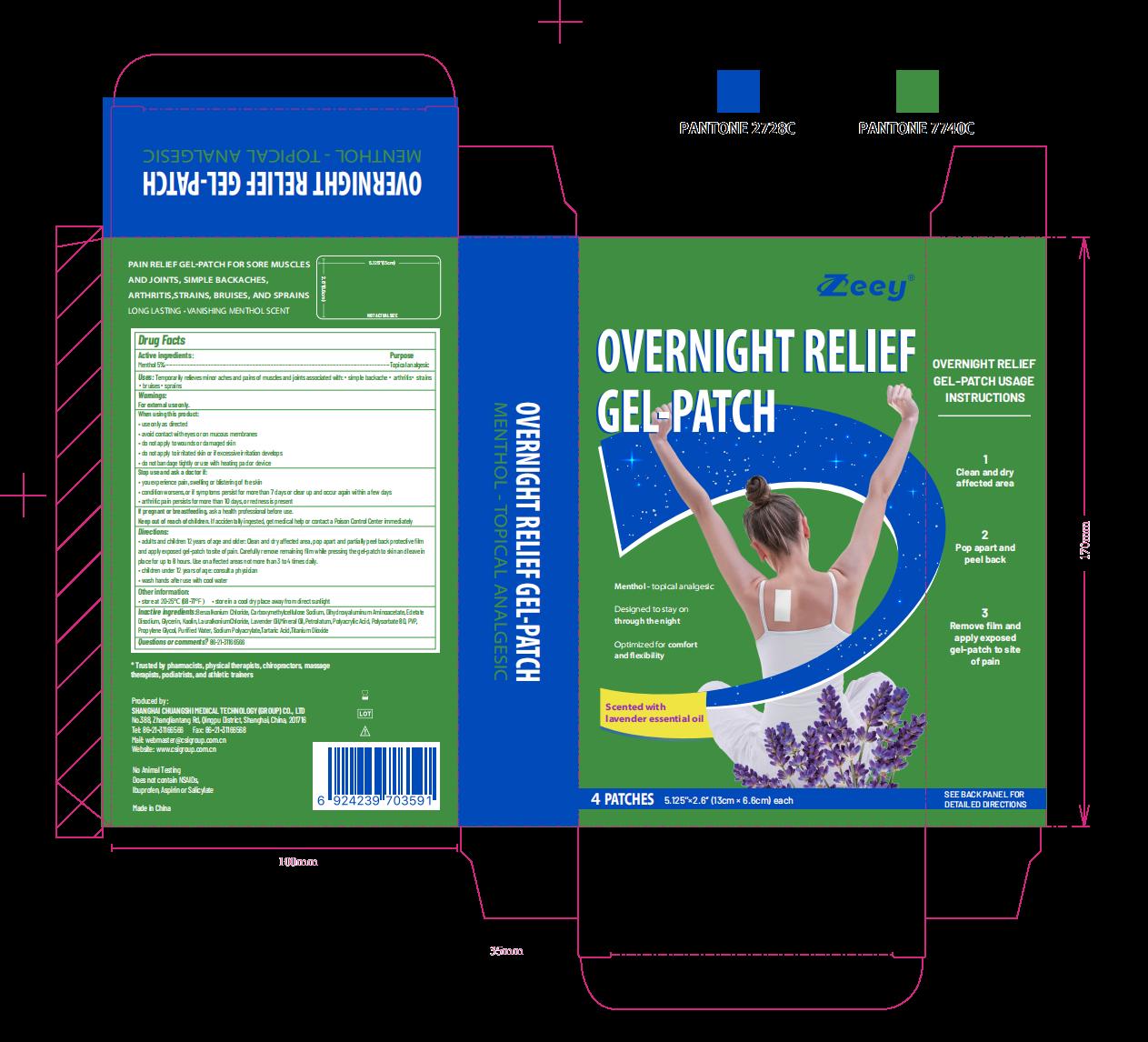 DRUG LABEL: OVERNIGHT RELIEF Gel-Patch
NDC: 73557-133 | Form: PATCH
Manufacturer: Shanghai Chuangshi Medical Technology (Group) Co., Ltd.
Category: otc | Type: HUMAN OTC DRUG LABEL
Date: 20241227

ACTIVE INGREDIENTS: MENTHOL 0.05 g/1 g
INACTIVE INGREDIENTS: KAOLIN 0.001 g/1 g; TARTARIC ACID 0.001 g/1 g; WATER 0.3095 g/1 g; DIHYDROXYALUMINUM AMINOACETATE ANHYDROUS 0.0015 g/1 g; PROPYLENE GLYCOL 0.06 g/1 g; POLYACRYLIC ACID (250000 MW) 0.2 g/1 g; CARBOXYMETHYLCELLULOSE SODIUM 0.001 g/1 g; SODIUM POLYACRYLATE (2500000 MW) 0.05 g/1 g; TITANIUM DIOXIDE 0.001 g/1 g; MINERAL OIL 0.03 g/1 g; PETROLATUM 0.002 g/1 g; BENZALKONIUM CHLORIDE 0.001 g/1 g; LAURALKONIUM CHLORIDE 0.001 g/1 g; POLYSORBATE 80 0.018 g/1 g; GLYCERIN 0.24 g/1 g; POVIDONE K90 0.012 g/1 g; LAVENDER OIL 0.02 g/1 g; EDETATE DISODIUM 0.001 g/1 g

CSI MENTHOL OVERNIGHT RELIEF GEL-PATCH, 5 Patches

Active ingredient

Menthol 5% w/w ...... Purpose: Topical analgesic

Purpose

Topical analgesic

Uses

Temporarily relieves minor aches and pains of muscles and joints associated with:

- simple backache
- arthrits
- strains
- bruises
- sprains

Warnings

For external use only

When using this prudocts:

• use only as directed
• avoid contact with eyes or on mucous membranes
• do not apply to wounds or damaged skin
• do not apply to irritated skin or if excessive irritation develops
• do not bandage tightly or use with heating pad or device

Stop use and ask a doctor if:
• you experience pain, swelling or blistering of the skin
• condition worsens, or if symptoms persist for more than 7 days or clear up and occur again within a few days
• arthritic pain persists for more than 10 days, or redness is present

If pregnant or breastfeeding,ask a health professional before use.

Keep out of reach of children.If accidentally ingested, get medical help or contact a Poison Control Center immediately

Ask doctor

Stop use and ask a doctor if:
• you experience pain, swelling or blistering of the skin
• condition worsens, or if symptoms persist for more than 7 days or clear up and occur again within a few days
• arthritic pain persists for more than 10 days, or redness is present

If pregnant or breastfeeding,ask a health professional before use.

When using

When using this prudocts:

• use only as directed
• avoid contact with eyes or on mucous membranes
• do not apply to wounds or damaged skin
• do not apply to irritated skin or if excessive irritation develops
• do not bandage tightly or use with heating pad or device

Do not use

• do not apply to wounds or damaged skin
• do not apply to irritated skin or if excessive irritation develops
• do not bandage tightly or use with heating pad or device

Stop use

Stop use and ask a doctor if: Burning disconfort or excessive skin irritation develops, condition worsens, or if symptoms persist for more than 7 days, or clear up and occur again within a few days

Pregnancy or breast feeding

If pregnant or breastfeeding,ask a health professional before use.

Keep out of reach of children

If accidentally ingested, get medical help or contact a Poison Control Center immediately

Directions

• adults and children 12 years of age and older: Clean and dry affected area, pop apart and partially peel back protective ﬁlm and apply exposed gel-patch to site of pain. Carefully remove remaining ﬁlm while pressing the gel-patch to skin and leave in place for up to 8 hours. Use on affected areas not more than 3 to 4 times daily.
• children under 12 years of age: consult a physician
• wash hands after use with cool water

Dosage forms & strengths

This is patch dosage form.

The active ingredient strength is 5%.

Inactive ingredients

Water, Glycerin, Polyacrylic Acid, Propylene Glycol, Sodium Polyacrylate, Mineral Oil, Lavender Essential Oil, Polysorbate 80, PVP, Petrolatum, Dihydroxyaluminum Aminoacetate, Edetate Disodium, Kaolin, Carboxymethylcellulose Sodium, Titanium Dioxide, L-Tartaric Acid, Benzalkonium Chloride, Lauralkonium Chloride

Questions or comments: 86-21-31166566

Other information

• store at 20-25℃ (68-77℉)

• store in a cool dry place away from direct sunlight